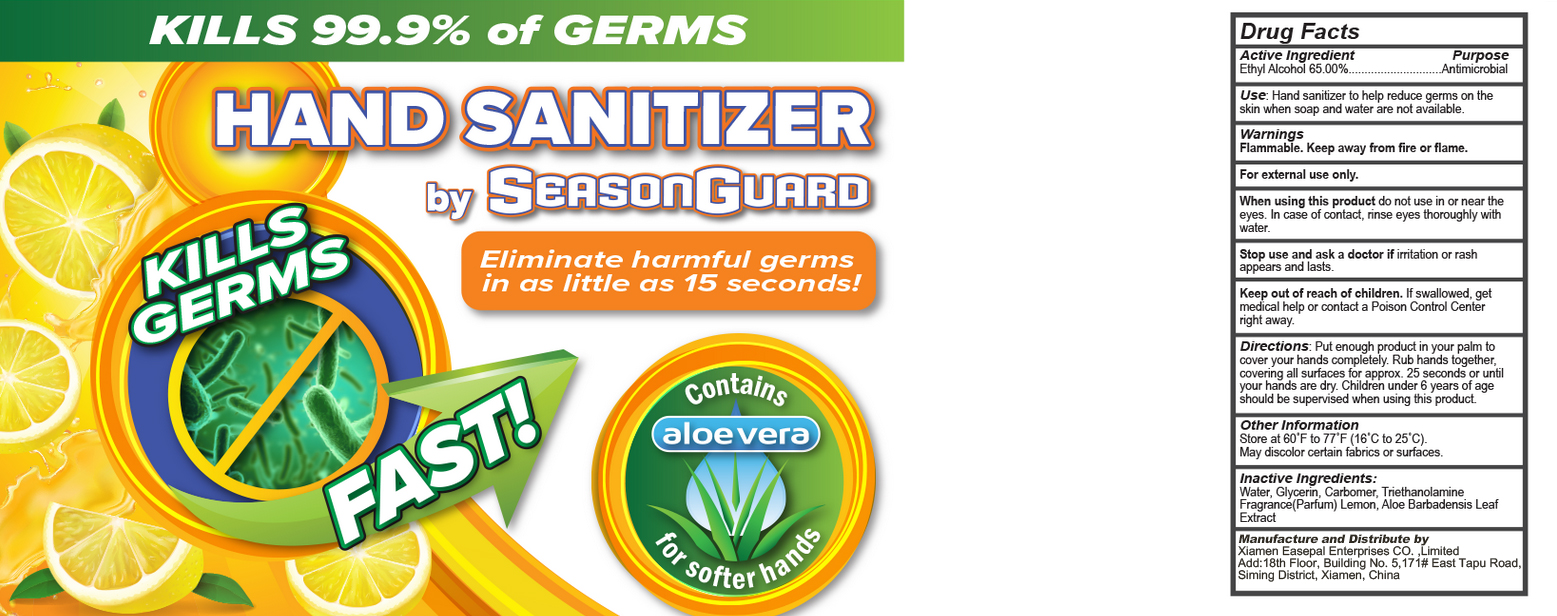 DRUG LABEL: aloe vera hand sanitizer
NDC: 67984-002 | Form: GEL
Manufacturer: XIAMEN EASEPAL ENTERPRISES LIMITED
Category: otc | Type: HUMAN OTC DRUG LABEL
Date: 20200330

ACTIVE INGREDIENTS: ALCOHOL 58.5 mL/90 mL
INACTIVE INGREDIENTS: CARBOMER HOMOPOLYMER, UNSPECIFIED TYPE; TROLAMINE; LEMON; FD&C RED NO. 4; D&C RED NO. 33; GLYCERIN; WATER; FD&C YELLOW NO. 5; FD&C BLUE NO. 1

WARNINGS

Flammable. Keep away from fire or flame.

INDICATIONS AND USAGE

Directions. Put enough product in your palm to cover your hands completely. Rub hands together, covering all surfaces for approx. 25 seconds or until your hands are dry. Children under 6 years of age should be supervised when using this product.

DOSAGE AND ADMINISTRATION

Store at 60'°F to 77°F (16°C to 25°C).

May discolor certain fabrics or surfaces.

PURPOSE

Disinfection
Sterilization
No Rinseing

INACTIVE INGREDIENT

Water, Glycerin, Carbomer, Triethanolamine.

Fragrance(Parfum) Lemon, Aloe Barbadensis Leaf Extract

ACTIVE INGREDIENT

Ethyl Alcohol 65.00%..

keep out of reach of children.